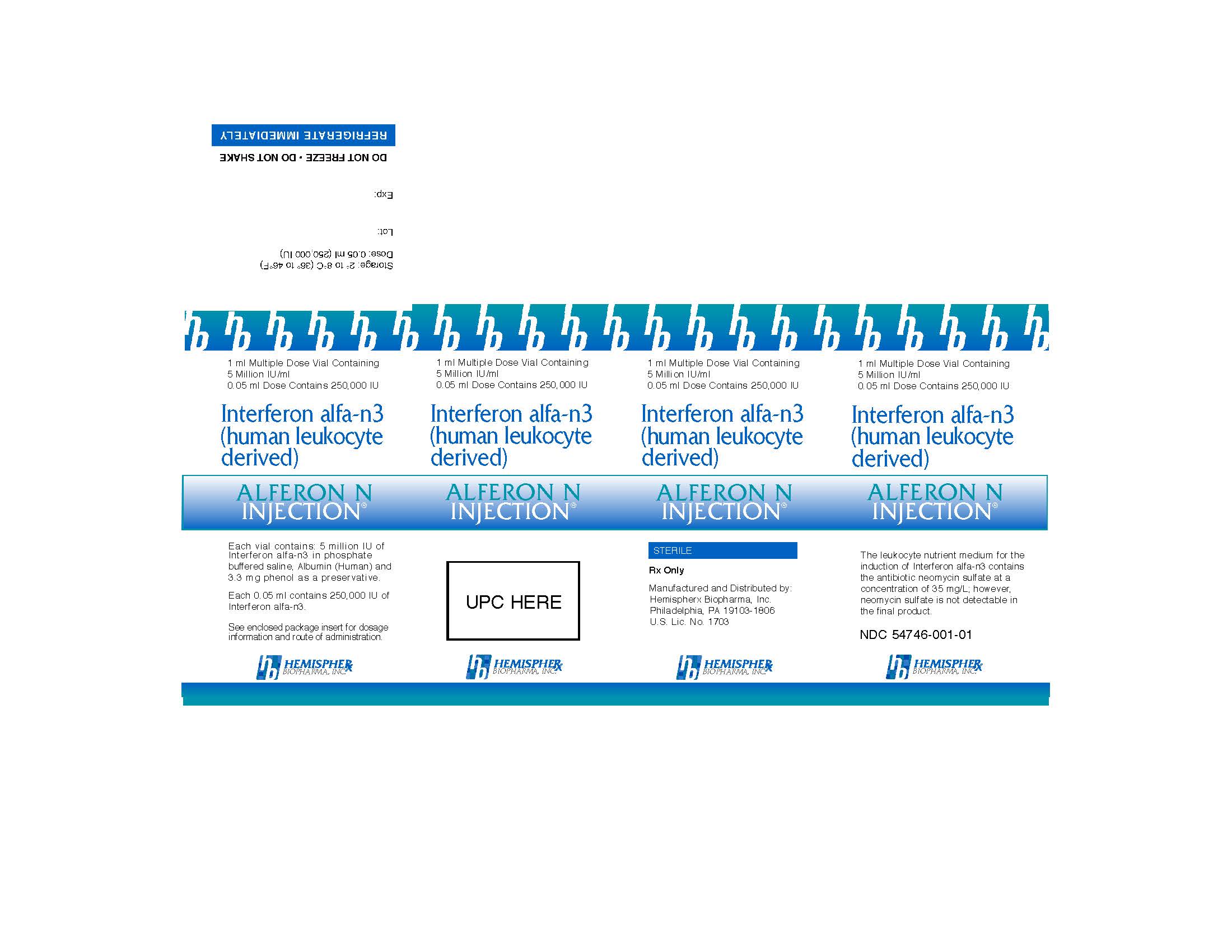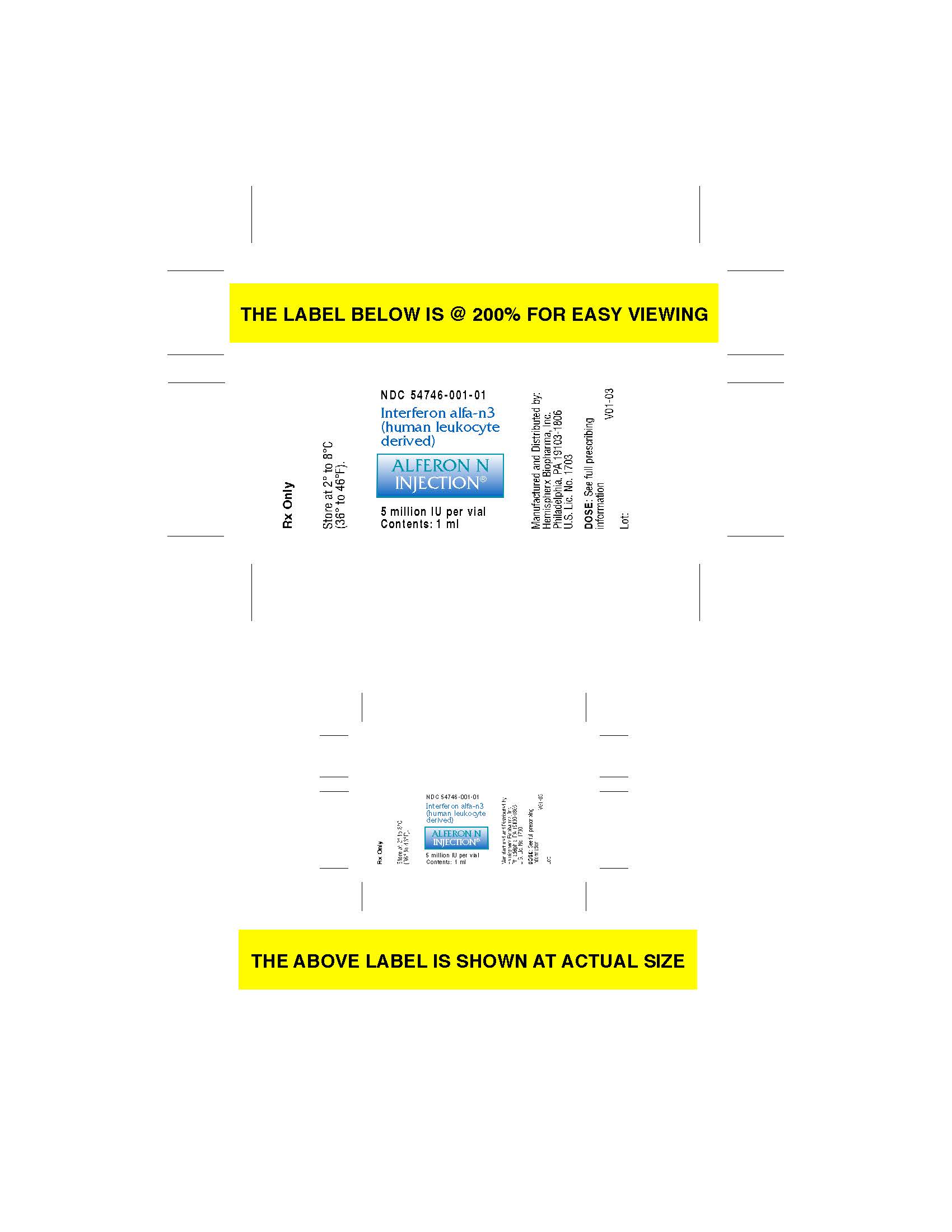 DRUG LABEL: Alferon
NDC: 54746-001 | Form: INJECTION
Manufacturer: AIM ImmunoTech Inc
Category: prescription | Type: HUMAN PRESCRIPTION DRUG LABEL
Date: 20211028

ACTIVE INGREDIENTS: INTERFERON ALFA-N3 5000000 [arb'U]/1 mL

Storage

STORAGE Alferon N Injection® [Interferon alfa-n3 (human leukocyte derived)] should be stored at 2º to 8ºC (36º to 46ºF). Do not Freeze. Do not shake.